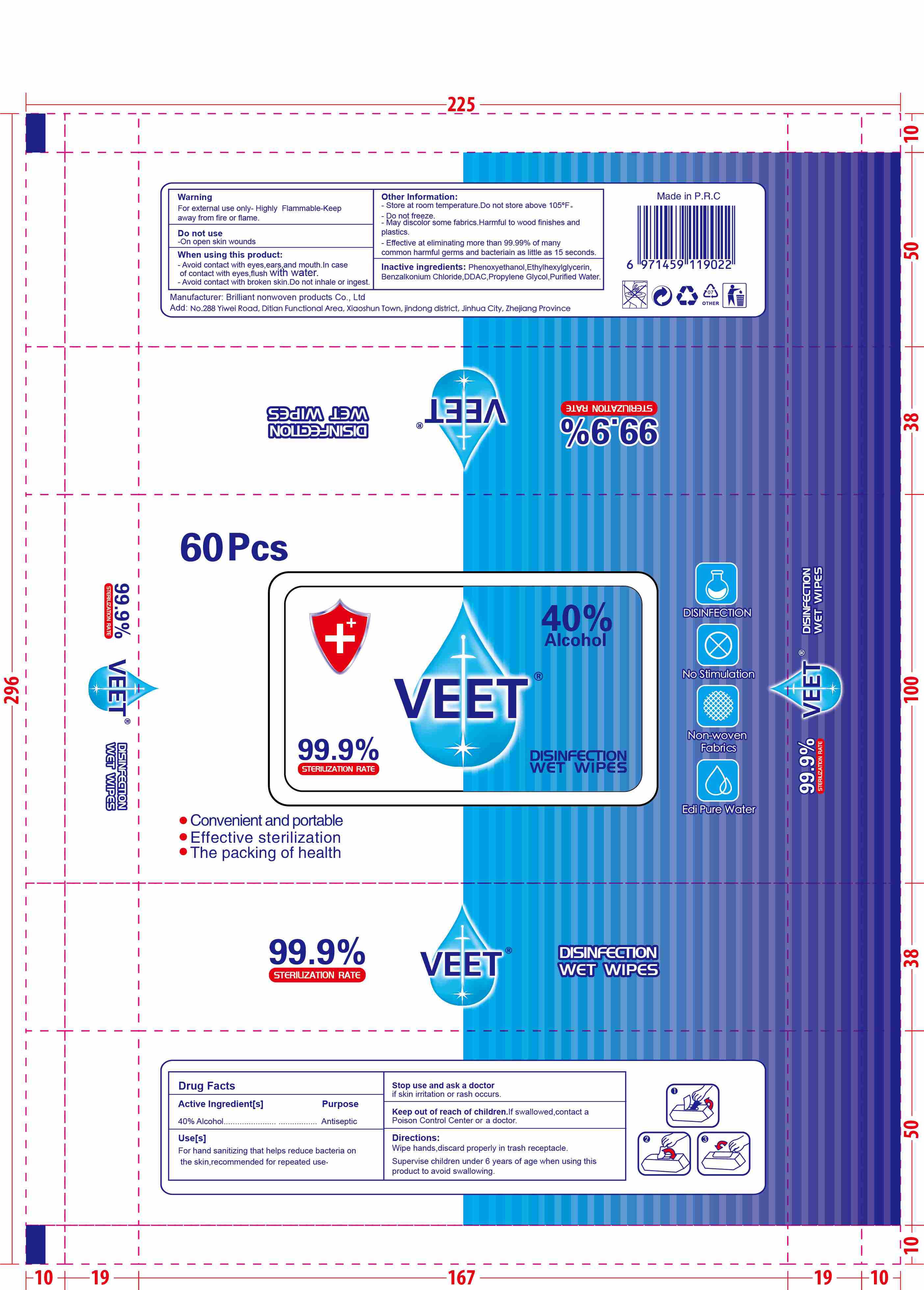 DRUG LABEL: veet disinfection wipes
NDC: 54016-001 | Form: CLOTH
Manufacturer: Jinhua Huihuang Non-woven Products Co., Ltd.
Category: otc | Type: HUMAN OTC DRUG LABEL
Date: 20200907

ACTIVE INGREDIENTS: ALCOHOL 90 mL/60 1
INACTIVE INGREDIENTS: PROPYLENE GLYCOL; WATER; GLYCERIN; DIDECYLDIMONIUM CHLORIDE; ETHYLHEXYLGLYCERIN; PHENOXYETHANOL; BENZALKONIUM CHLORIDE

DOSAGE AND ADMINISTRATION

Store at room temperature.Do not store above 105°F .Do not freeze.

INACTIVE INGREDIENT

Phenoxyethanol, Ethylhexylglycerin,Benzalkonium Chloride ,DDAC,Propylene Glycol,Purified Water,Glycerin

INDICATIONS AND USAGE

Open the package and take out the paper towel to wipe

ACTIVE INGREDIENT

ALCOHOL

keep out of reach of children

PURPOSE

Disinfection
Sterilization
No Rinseing

WARNINGS

For external use only- Highly Flammable,Keep away from fire or flame.